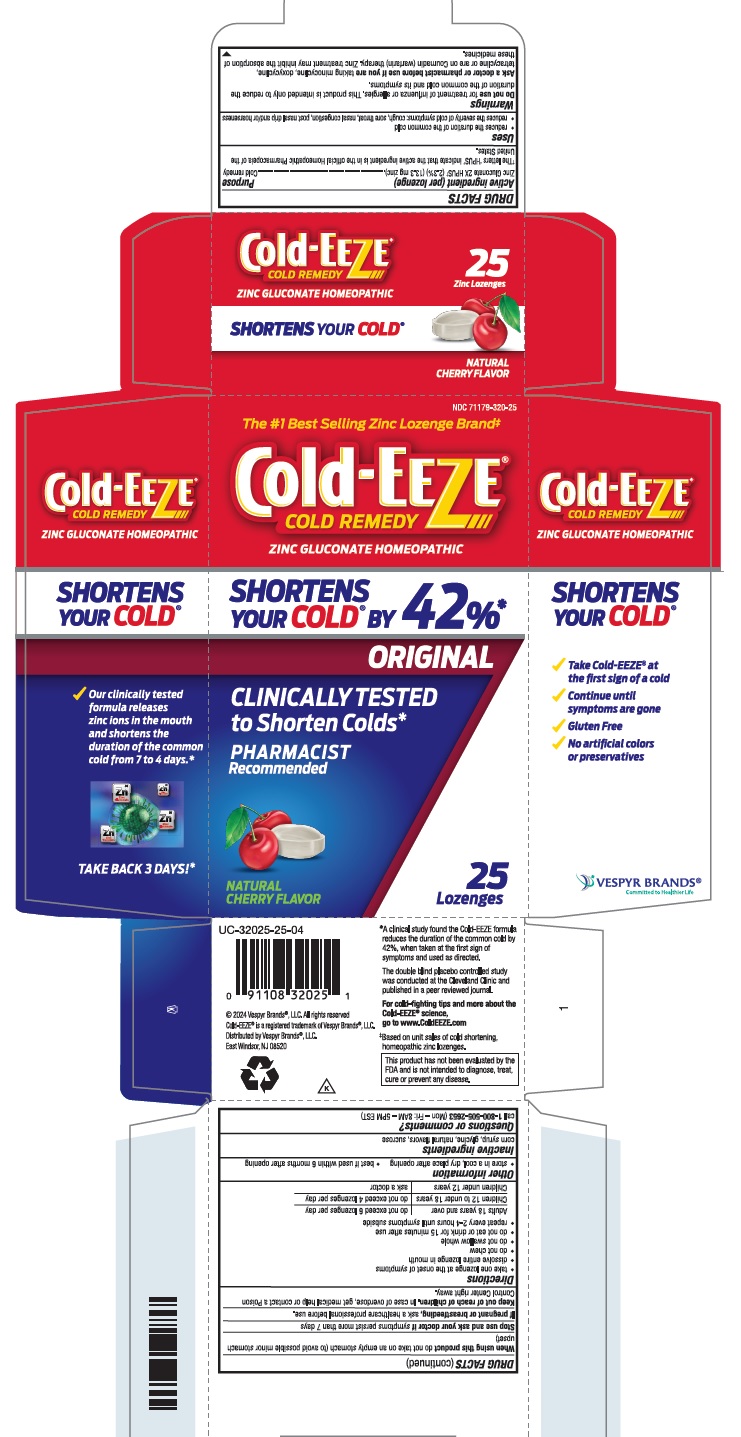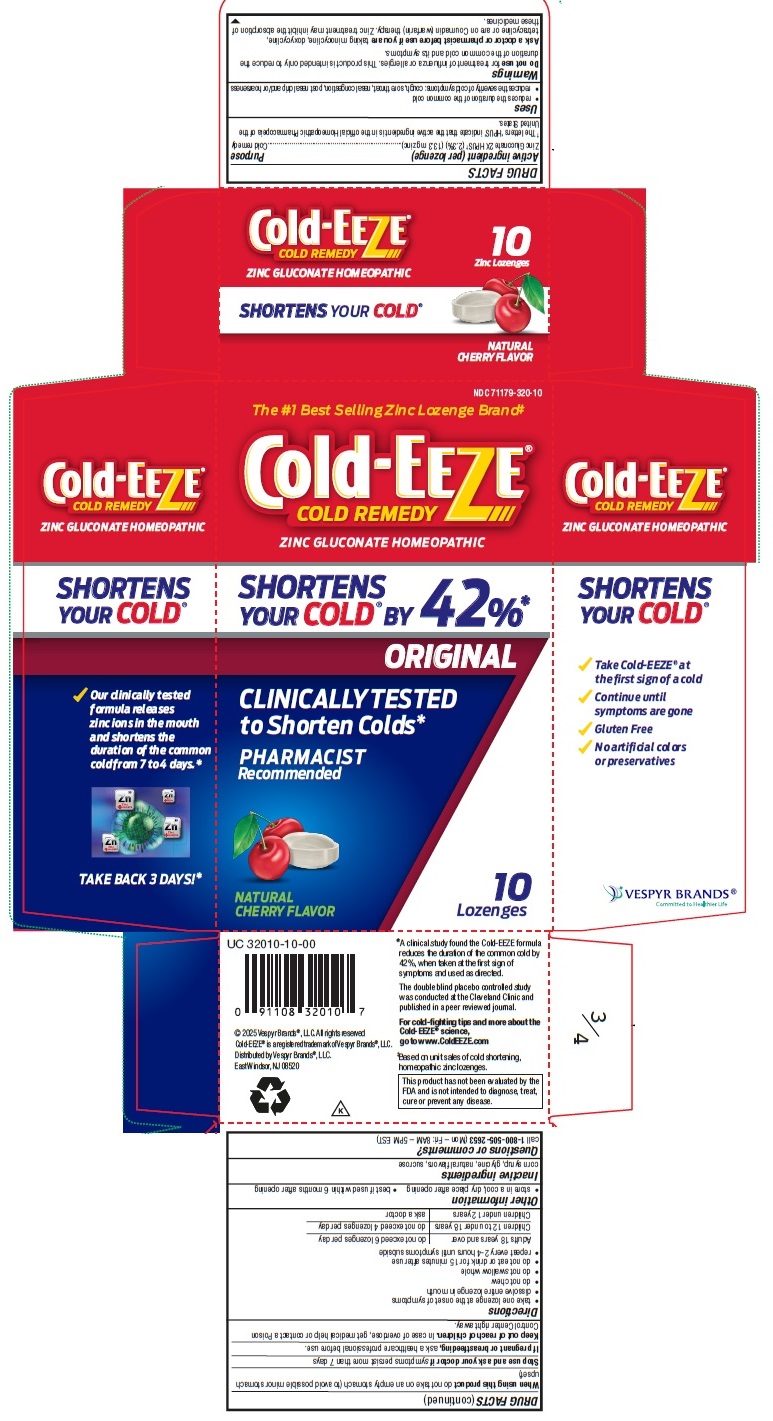 DRUG LABEL: Cold-EEZE Cold Remedy
NDC: 71179-320 | Form: LOZENGE
Manufacturer: Vespyr Brands Inc
Category: homeopathic | Type: HUMAN OTC DRUG LABEL
Date: 20251202

ACTIVE INGREDIENTS: ZINC GLUCONATE 13.3 mg/1 1
INACTIVE INGREDIENTS: GLYCINE; SUCROSE; CORN SYRUP

Cold-EEZE Cold Remedy

Active ingredient

Active ingredient (per lozenge)
Zinc Gluconate 2X HPUS† (2.3%) (13.3 mg zinc)
† The letters ‘HPUS’ indicate that the active ingredient is in the official Homeopathic Pharmacopeia of the United States.

Purposes

Cold remedy

Uses

- reduces the duration of the common cold
- reduces the severity of cold symptoms: cough, sore throat, nasal congestion, post nasal drip and/or hoarseness

Warnings

Do not use for treatment of influenza or allergies. This product is intended only to reduce the duration of the common cold and its symptoms.

Ask a doctor or pharmacist before use if you are taking minocycline, doxycycline, tetracycline or are on Coumadin (warfarin) therapy. Zinc treatment may inhibit the absorption of these medicines.

When using this product do not take on an empty stomach (to avoid possible minor stomach upset)

Stop use and ask your doctor if symptoms persist more than 7 days

PREGNANCY OR BREAST FEEDING

If pregnant or breastfeeding, ask a healthcare professional before use.

Keep out of reach of children. In case of overdose, get medical help or contact a Poison Control Center right away.

Directions

• take one lozenge at the onset of symptoms
• dissolve entire lozenge in mouth

• do not chew

• do not swallow whole
• do not eat or drink for 15 minutes after use
• repeat every 2-4 hours until symptoms subside

Adults 18 years and over | do not exceed 6 lozenges per day
Children 12 to under 18 years | do not exceed 4 lozenges per day
Children under 12 years | ask a doctor before use

Other information

- store in a cool, dry place after opening
- best if used within 6 months after opening

Inactive ingredients

corn syrup, glycine, natural flavors, sucrose

Questions?

call 1-800-505-2653 (Mon – Fri: 8AM – 5PM EST)

25 ct package

Cold-EEZE®

COLD REMEDY

ZINC GLUCONATE HOMEOPATHIC

SHORTENS YOUR COLD® BY 42%*

ORIGINAL

CLINICALLY TESTED to Shorten Colds*

PHARMACIST Recommended

NATURAL CHERRY FLAVOR

25 Zinc Lozenges

©2024 Vespyr Brands®, LLC

Cold-EEZE® is a registred trademark of Vespyr Brands®, LLC

Distributed by Vespyr Brands®, LLC

East Windsor, NJ 08520

This product has not been evaluated by the FDA

*A clinical study found the Cold-EEZE formula reduces the duration of the common cold by 42%, when taken at the first sign of symptoms and used as directed.

The double blind placebo controlled study was conducted at the Cleveland Clinic and published in a peer reviewed journal.

10 ct package

Cold-EEZE®

COLD REMEDY

ZINC GLUCONATE HOMEOPATHIC

SHORTENS YOUR COLD® BY 42%*

ORIGINAL

CLINICALLY TESTED to Shorten Colds*

PHARMACIST Recommended

NATURAL CHERRY FLAVOR

10 Lozenges

©2025 Vespyr Brands®, Inc.

Cold-EEZE® is a registred trademark of Vespyr Brands®, LLC

Distributed by Vespyr Brands®, LLC

East Windsor, NJ 08520

This product has not been evaluated by the FDA and is not intended to diagnose, treat, cure, or prevent any disease.

*A clinical study found the Cold-EEZE formula reduces the duration of the common cold by 42%, when taken at the first sign of symptoms and used as directed.

The double blind placebo controlled study was conducted at the Cleveland Clinic and published in a peer reviewed journal.